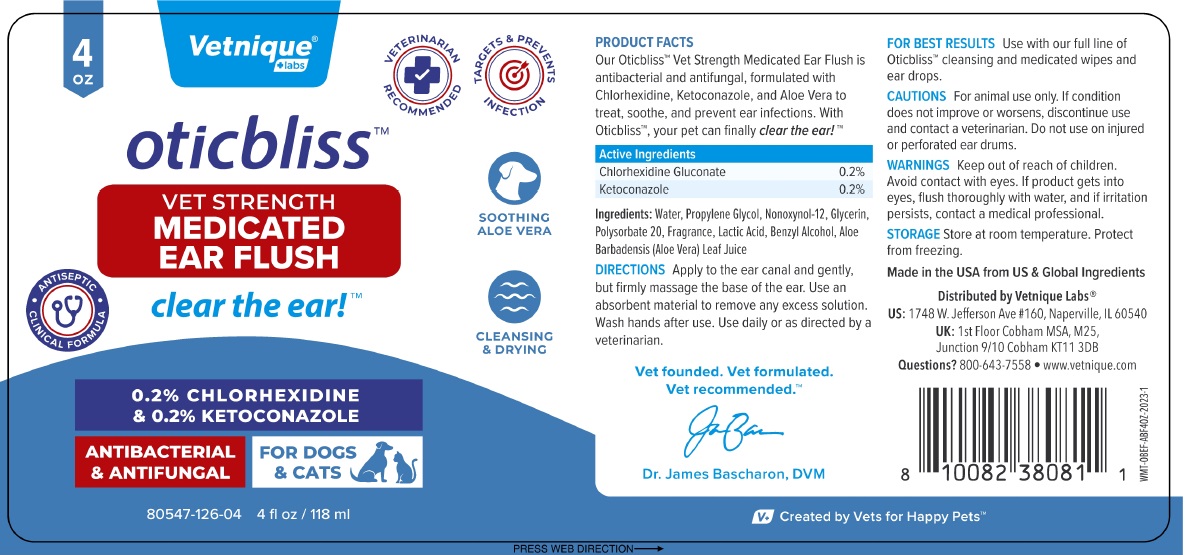 DRUG LABEL: oticbliss VET STRENGTH MEDICATED EAR FLUSH
NDC: 80547-126 | Form: SOLUTION
Manufacturer: Vetnique Labs LLC
Category: animal | Type: OTC ANIMAL DRUG LABEL
Date: 20231226

ACTIVE INGREDIENTS: CHLORHEXIDINE GLUCONATE 2 mg/1 mL; KETOCONAZOLE 2 mg/1 mL
INACTIVE INGREDIENTS: WATER; PROPYLENE GLYCOL; NONOXYNOL-12; GLYCERIN; POLYSORBATE 20; LACTIC ACID, UNSPECIFIED FORM; BENZYL ALCOHOL; ALOE VERA LEAF

oticbliss™ VET STRENGTH MEDICATED EAR FLUSH

PRODUCT FACTS

Our Oticbliss™ Vet Strength Medicated Ear Flush is antibacterial and antifungal, formulated with Chlorhexidine, Ketoconazole and Aloe Vera to treat, soothe, and prevent ear infections. With Oticbliss™, your pet can finally clear the ear! ™

Active Ingredients

Chlorhexidine Gluconate 0.2%
Ketoconazole 0.2%

Ingredients:

Water, Propylene Glycol, Nonoxynol-12, Glycerin, Polysorbate 20, Fragrance, Lactic Acid, Benzyl Alcohol, Aloe Barbadensis (Aloe Vera) Leaf Juice

DIRECTIONS

Apply to the ear canal and gently, but firmly massage the base of the ear. Use an absorbent material to remove any excess solution. Wash hands after use. Use daily or as directed by a veterinarian.

FOR BEST RESULTS Use with our full line of Oticbliss™ cleansing and medicated wipes and ear drops.

CAUTIONS

For animal use only. If condition does not improve or worsens, discontinue use and contact a veterinarian. Do not use on injured or perforated ear drums.

WARNINGS

Keep out of reach of children. Avoid contact with eyes. If product gets into eyes, flush thoroughly with water, and if irritation persists, contact a medical professional.

STORAGE

Store at room temperature. Protect from freezing.

VETERINARIAN RECOMMENDED

TARGETS & PREVENTS INFECTION

ANTISEPTIC CLINICAL FORMULA

SOOTHING ALOE VERA

CLEANSING & DRYING

FOR DOGS & CATS

Vet founded. Vet formulated.
Vet recommended.™

Made in the USA from US & Global Ingredients

Distributed by Vetnique Labs®
US: 1748 W. Jefferson Ave #160, Naperville, IL 60540
UK: 1st Floor Cobham MSA, M25, Junction 9/10 Cobham KT11 3DB qw

Questions? 800-643-7558 • www.vetnique.com

V+ Created by Vets for Happy Pets™